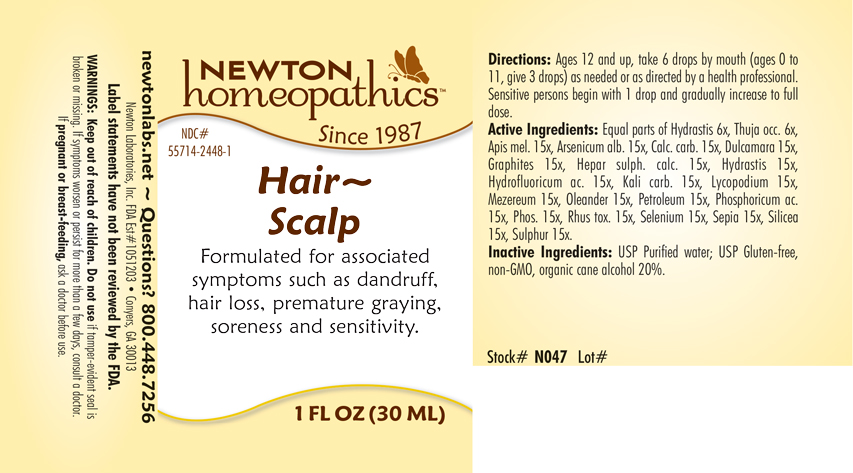 DRUG LABEL: Hair-Scalp
NDC: 55714-2448 | Form: LIQUID
Manufacturer: Newton Laboratories, Inc.
Category: homeopathic | Type: HUMAN OTC DRUG LABEL
Date: 20201130

ACTIVE INGREDIENTS: APIS MELLIFERA 15 [hp_X]/1 mL; ARSENIC TRIOXIDE 15 [hp_X]/1 mL; OYSTER SHELL CALCIUM CARBONATE, CRUDE 15 [hp_X]/1 mL; SOLANUM DULCAMARA TOP 15 [hp_X]/1 mL; GRAPHITE 15 [hp_X]/1 mL; CALCIUM SULFIDE 15 [hp_X]/1 mL; GOLDENSEAL 15 [hp_X]/1 mL; HYDROFLUORIC ACID 15 [hp_X]/1 mL; POTASSIUM CARBONATE 15 [hp_X]/1 mL; LYCOPODIUM CLAVATUM SPORE 15 [hp_X]/1 mL; DAPHNE MEZEREUM BARK 15 [hp_X]/1 mL; NERIUM OLEANDER LEAF 15 [hp_X]/1 mL; KEROSENE 15 [hp_X]/1 mL; PHOSPHORIC ACID 15 [hp_X]/1 mL; PHOSPHORUS 15 [hp_X]/1 mL; TOXICODENDRON PUBESCENS LEAF 15 [hp_X]/1 mL; SELENIUM 15 [hp_X]/1 mL; SEPIA OFFICINALIS JUICE 15 [hp_X]/1 mL; SILICON DIOXIDE 15 [hp_X]/1 mL; SULFUR 15 [hp_X]/1 mL; THUJA OCCIDENTALIS LEAFY TWIG 6 [hp_X]/1 mL
INACTIVE INGREDIENTS: ALCOHOL; WATER

Hair 2448L

INDICATIONS & USAGE SECTION

Formulated for associated symptoms such as dandruff, hair loss, premature graying, soreness and sensitivity.

DOSAGE & ADMINISTRATION SECTION

Directions: Ages 12 and up, take 6 drops by mouth (ages 0 to 11, give 3 drops) as needed or as directed by a health professional. Sensitive persons begin with 1 drop and gradually increase to full dose.

.

OTC - ACTIVE INGREDIENT SECTION

Equal parts of Hydrastis 6x, Thuja occ. 6x, Apis mel. 15x, Arsenicum alb. 15x, Calc.carb. 15x, Dulcamara 15x, Graphites 15x, Hepar sulph. calc. 15x, Hydrastis 15x, Hydrofluoricum acidum 15x, Kali carb. 15x, Lycopodium 15x, Mezereum 15x, Oleander 15x, Petroleum 15x, Phosphoricum ac. 15x, Phosphorus 15x, Rhus toxicodendron 15x, Selenium 15x, Sepia 15x, Silicea 15x, Sulphur 15x.

OTC - PURPOSE SECTION

Formulated for associated symptoms such as dandruff, hair loss, premature graying, soreness and sensitivity.

INACTIVE INGREDIENT SECTION

Inactive Ingredients: USP Purified Water; USP Gluten-free, non-GMO, organic cane alcohol 20%.

QUESTIONS SECTION

newtonlabs.net – Questions? 800.448.7256

Newton Laboratories, Inc. FDA Est # 1051203 - Conyers, GA 30013

WARNINGS SECTION

WARNINGS: Keep out of reach of children. Do not use if tamper-evident seal is broken or missing. If symptoms worsen or persist for more than a few days, consult a doctor. If p regnant or breast-feeding, ask a doctor before use.

OTC - PREGNANCY OR BREAST FEEDING SECTION

If pregnant or breast-feeding, ask a doctor before use.

OTC - KEEP OUT OF REACH OF CHILDREN SECTION

Keep out of reach of children.